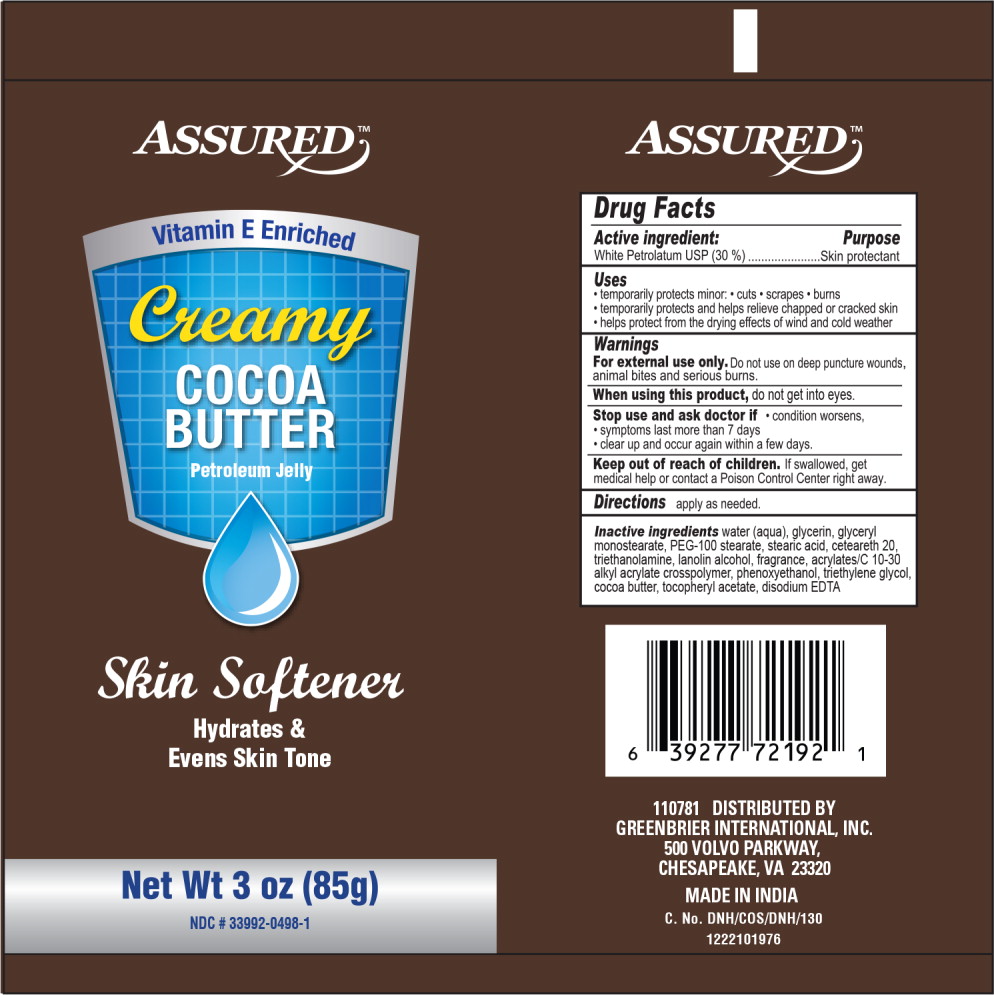 DRUG LABEL: Petrolatum
NDC: 33992-0498 | Form: CREAM
Manufacturer: Greenbrier International, Inc.
Category: otc | Type: HUMAN OTC DRUG LABEL
Date: 20190517

ACTIVE INGREDIENTS: Petrolatum 30 g/100 g
INACTIVE INGREDIENTS: Water; GLYCERIN; GLYCERYL MONOSTEARATE; PEG-100 STEARATE; STEARIC ACID; POLYOXYL 20 CETOSTEARYL ETHER; TROLAMINE; LANOLIN ALCOHOLS; CARBOMER COPOLYMER TYPE A (ALLYL PENTAERYTHRITOL CROSSLINKED); PHENOXYETHANOL; TRIETHYLENE GLYCOL; COCOA BUTTER; .ALPHA.-TOCOPHEROL ACETATE; EDETATE DISODIUM

ASSURED™
Drug Facts

Active Ingredient:

White Petrolatum USP (30 %)

Purpose

Skin protectant

Uses

- temporarily protects minor:
  - cuts
  - scrapes
  - burns
- temporarily protects and helps relieve chapped or cracked skin
- helps protect from the drying effects of wind and cold weather

Warnings

For external use only.

Do not use on deep puncture wounds, animal bites and serious burns.

When using this product,

do not get into eyes

Stop use and ask doctor if

- condition worsens,
- symptoms last more than 7 days
- clear up and occur again within a few days

Keep out of reach of children.

If swallowed, get medical help or contact a Poison Control Center right away.

Directions

apply as needed.

Inactive ingredients

water (aqua), glycerin, glyceryl monostearate, PEG-100 stearate, stearic acid, ceteareth 20, trieathanolamine, lanolin alcohol, fragrance, acrylates/C 10-30 alkyl acrylate crosspolymer, phenoxyethanol, triethylene glycol, cocoa butter, tocopheryl acetate, disodium EDTA

110781 DISTRIBUTED BY

GREENBRIER INTERNATIONAL, INC.

500 VOLVO PARKWAY,

CHESAPEAKE, VA 23320

MADE IN INDIA

Skin Softener

Hydrates &

Evens Skin Tone

COCOA

BUTTER

Petroleum Jelly

C. No. DNH/COS/DNH/130

1222101976

Principal Display Panel - 3 oz Tube Label

ASSURED™

Vitamin E Enriched

Creamy

COCOA
BUTTER

Petroleum Jelly

Skin Softener

Hydrates &
Evens Skin Tone

Net Wt 3 oz (85g)

NDC # 33992-0498-1